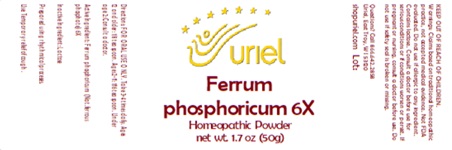 DRUG LABEL: Ferrum phosphoricum 6
NDC: 48951-4059 | Form: POWDER
Manufacturer: Uriel Pharmacy Inc.
Category: homeopathic | Type: HUMAN OTC DRUG LABEL
Date: 20250627

ACTIVE INGREDIENTS: FERROSOFERRIC PHOSPHATE 6 [hp_X]/1 g
INACTIVE INGREDIENTS: LACTOSE

Ferrum phosphoricum 6

INDICATIONS AND USAGE

Directions: FOR ORAL USE ONLY.

DOSAGE AND ADMINISTRATION

Take 3-4 times daily. Ages 12 and older: 1/8 teaspoon. Ages 2-11: 1/16 teaspoon. Under age 2: Consult a doctor.

Active Ingredient: Ferrum phosphoricum (Nat. ferrous phosphate) 6X

Inactive Ingredient: Lactose

Prepared using rhythmical processes.

PURPOSE

Use: Temporary relief of cough.

KEEP OUT OF REACH OF CHILDREN.

WARNINGS

Warnings: Claims based on traditional homeopathic practice, not accepted medical evidence. Not FDA evaluated. Do not use if allergic to any ingredient. Contains lactose. Consult a doctor before use for serious conditions or if conditions worsen or persist. If pregnant or nursing, consult a doctor before use. Do not use if safety seal is broken or missing.

Questions? Call 866.642.2858
Uriel, East Troy, WI 53120
shopuriel.com Lot: